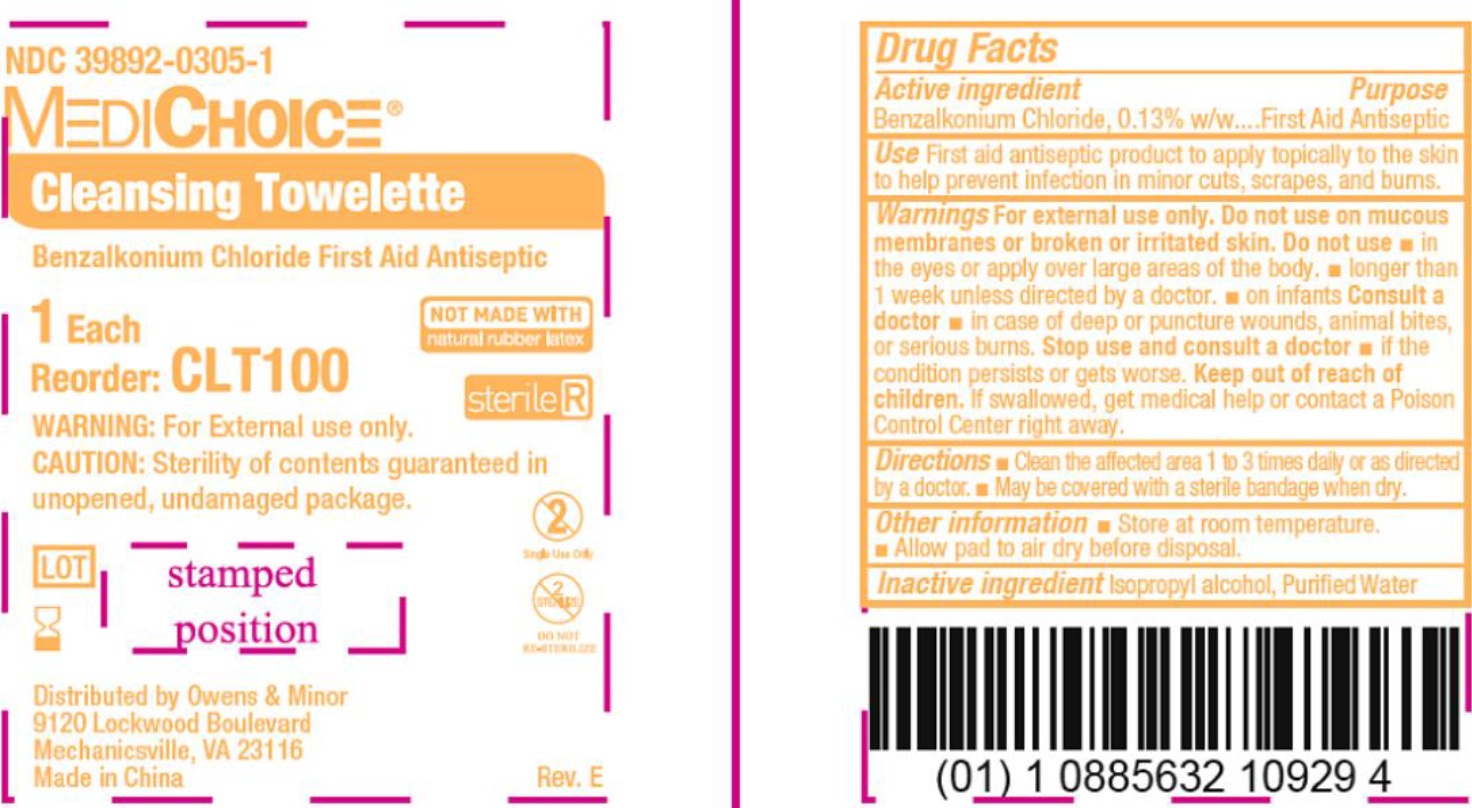 DRUG LABEL: MediChoice Cleansing
NDC: 39892-0305 | Form: CLOTH
Manufacturer: O&M HALYARD, INC.
Category: otc | Type: HUMAN OTC DRUG LABEL
Date: 20251008

ACTIVE INGREDIENTS: BENZALKONIUM CHLORIDE 0.13 g/100 g
INACTIVE INGREDIENTS: ISOPROPYL ALCOHOL; WATER

MediChoice Cleansing Towelette

Active ingredient

Benzalkonium Chloride, 0.13% w/w

Purpose

First Aid Antiseptic

Use

First aid antiseptic product to apply topically to the skin to help prevent infection in minor cuts, scrapes, and burns.

Warnings

For external use only on mucouse membranes or broken or irritated skin.

Do not use

- in the eyes or apply over large areas of the body.
- longer than 1 week unless directed by a doctor.
- no infants. Consult a doctor
- in case of deep or punture wounds, animal bites, or serious burns.

Stop use and consult a doctor

If the condition persists or gets worse.

Keep out of reach of children.

If swallowed, get medical help or contact a Poison control Center right away.

Directions

- Clean the affected area 1 to 3 times daily or as directed by a doctor. May be covered with a sterile bandage when dry.

Other information

- Store at room temperature.
- Allow pad to air dry before disposal.

Inactive ingredient

Isopropyl alcohol, Purified Water